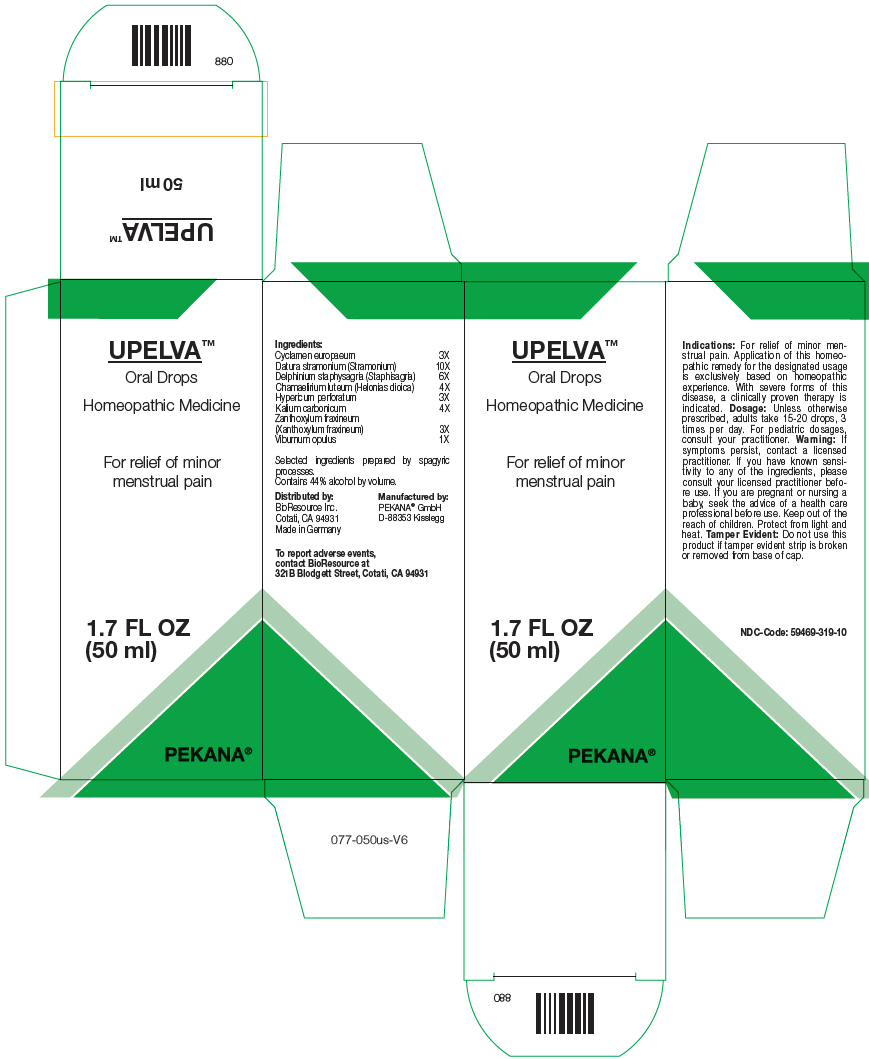 DRUG LABEL: UPELVA
NDC: 59469-319 | Form: SOLUTION/ DROPS
Manufacturer: PEKANA Naturheilmittel GmbH
Category: homeopathic | Type: HUMAN OTC DRUG LABEL
Date: 20230111

ACTIVE INGREDIENTS: CYCLAMEN PURPURASCENS TUBER 3 [hp_X]/50 mL; CHAMAELIRIUM LUTEUM ROOT 4 [hp_X]/50 mL; HYPERICUM PERFORATUM WHOLE 3 [hp_X]/50 mL; POTASSIUM CARBONATE 4 [hp_X]/50 mL; DELPHINIUM STAPHISAGRIA SEED 6 [hp_X]/50 mL; DATURA STRAMONIUM FLOWERING TOP 10 [hp_X]/50 mL; VIBURNUM OPULUS BARK 1 [hp_X]/50 mL; ZANTHOXYLUM AMERICANUM BARK 3 [hp_X]/50 mL
INACTIVE INGREDIENTS: WATER; ALCOHOL

UPELVA™

ACTIVE INGREDIENT

Ingredients:
Cyclamen europaeum | 3X
Datura stramonium (Stramonium) | 10X
Delphinium staphysagria (Staphisagria) | 6X
Chamaelirium luteum (Helonias dioica) | 4X
Hypericum perforatum | 3X
Kalium carbonicum | 4X
Zanthoxylum fraxineum (Xanthoxylum fraxineum) | 3X
Viburnum opulus | 1X

Selected ingredients prepared by spagyric processes.

INACTIVE INGREDIENT

Contains 44% alcohol by volume.

Indications

PURPOSE

For relief of minor menstrual pain. Application of this homeopathic remedy for the designated usage is exclusively based on homeopathic experience. With severe forms of this disease, a clinically proven therapy is indicated.

Dosage

Unless otherwise prescribed, adults take 15-20 drops, 3 times per day. For pediatric dosages, consult your practitioner.

Warning

If symptoms persist, contact a licensed practitioner. If you have known sensitivity to any of the ingredients, please consult your licensed practitioner before use. If you are pregnant or nursing a baby, seek the advice of a health care professional before use.

Keep out of the reach of children.

STORAGE AND HANDLING

Protect from light and heat.

Tamper Evident

Do not use this product if tamper evident strip is broken or removed from base of cap.

QUESTIONS

To report adverse events, contact BioResource at 321B Blodgett Street, Cotati, CA 94931

Distributed by:
BioResource Inc.
Cotati, CA 94931

Manufactured by:
PEKANA® GmbH
D-88353 Kisslegg

PRINCIPAL DISPLAY PANEL - 50 ml Bottle Box

UPELVA™

Oral Drops

Homeopathic Medicine

For relief of minor
menstrual pain

1.7 FL OZ
(50 ml)

PEKANA®